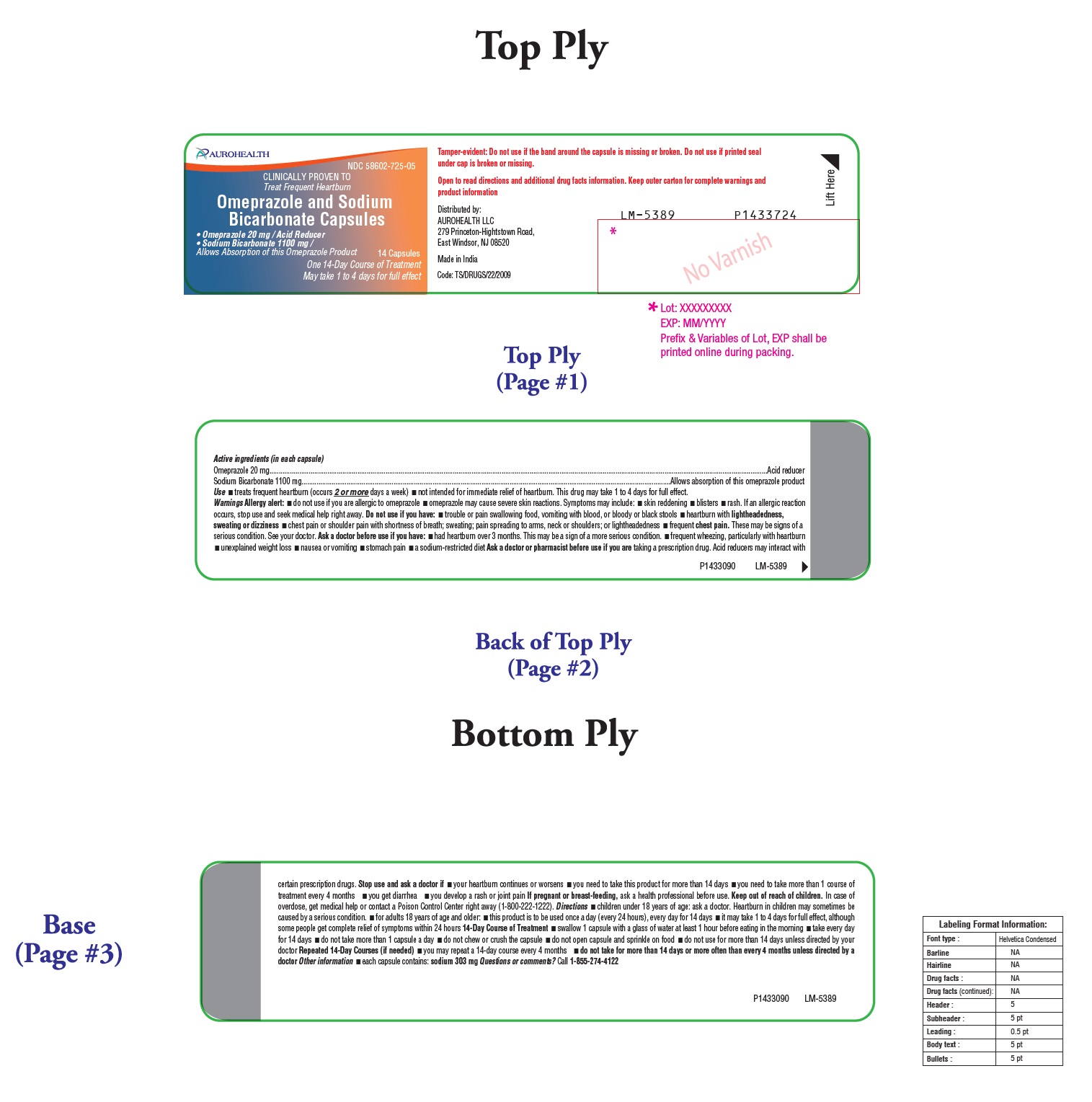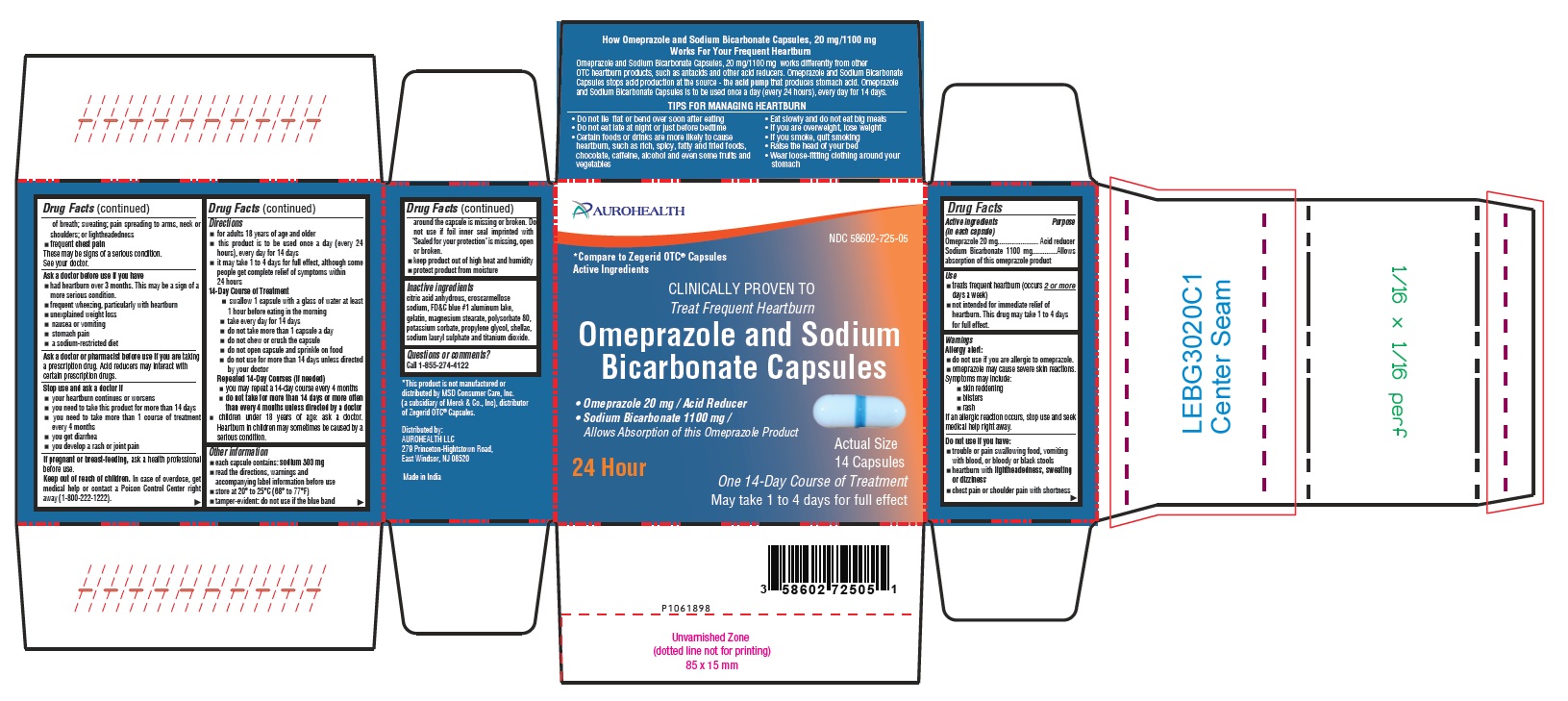 DRUG LABEL: OMEPRAZOLE AND SODIUM BICARBONATE
NDC: 58602-725 | Form: CAPSULE
Manufacturer: Aurohealth LLC
Category: otc | Type: Human OTC Drug Label
Date: 20251204

ACTIVE INGREDIENTS: OMEPRAZOLE 20 mg/1 1; SODIUM BICARBONATE 1100 mg/1 1
INACTIVE INGREDIENTS: ANHYDROUS CITRIC ACID; CROSCARMELLOSE SODIUM; FD&C BLUE NO. 1 ALUMINUM LAKE; GELATIN, UNSPECIFIED; MAGNESIUM STEARATE; POLYSORBATE 80; POTASSIUM SORBATE; PROPYLENE GLYCOL; SHELLAC; SODIUM LAURYL SULFATE; TITANIUM DIOXIDE

Active ingredients (in each capsule)

Omeprazole 20 mg
Sodium Bicarbonate 1100 mg

Purpose

Acid reducer
Allows absorption of this omeprazole product

Use

- treats frequent heartburn (occurs 2 or more days a week)
- not intended for immediate relief of heartburn. This drug may take 1 to 4 days for full effect

Warnings

Allergy alert:
• do not use if you are allergic to omeprazole.

• omeprazole may cause severe skin reactions.
Symptoms may include:

• skin reddening
• blisters
• rash
If an allergic reaction occurs, stop use and seek medical help right away.

Do not use if you have:

- trouble or pain swallowing food, vomiting with blood, or bloody or black stools
- heartburn with lightheadedness, sweating or dizziness
- chest pain or shoulder pain with shortness of breath; sweating; pain spreading to arms, neck or shoulders; or lightheadedness
- frequent chest pain

These may be signs of a serious condition. See your doctor.

Ask a doctor before use if you have:

- had heartburn over 3 months. This may be a sign of a more serious condition.
- frequent wheezing, particularly with heartburn
- unexplained weight loss
- nausea or vomiting
- stomach pain
- a sodium-restricted diet

Ask a doctor or pharmacist before use if you are taking a prescription drug.

Acid reducers may interact with certain prescription drugs.

Stop use and ask a doctor if:

- your heartburn continues or worsens
- you need to take this product for more than 14 days
- you need to take more than 1 course of treatment every 4 months
- you get diarrhea
- you develop a rash or joint pain

If pregnant or breast-feeding,

ask a health professional before use.

Keep out of reach of children.

In case of overdose, get medical help or contact a Poison Control Center right away (1-800-222-1222).

Directions

- for adults 18 years of age and older
- this product is to be used once a day (every 24 hours), every day for 14 days
- it may take 1 to 4 days for full effect; although some people get complete relief of symptoms within 24 hours

14-Day Course of Treatment

- swallow 1 capsule with a glass of water at least 1 hour before eating in the morning
- take every day for 14 days
- do not take more than 1 capsule a day
- do not chew or crush the capsule
- do not open capsule and sprinkle on food
- do not use for more than 14 days unless directed by your doctor

Repeated 14-Day Courses (if needed)

- you may repeat a 14-day course every 4 months
- do not take for more than 14 days or more often than every 4 months unless directed by a doctor
- children under 18 years of age: ask a doctor. Heartburn in children may sometimes be caused by a serious condition.

Other information

- each capsule contains: sodium 303 mg
- read the directions, warnings and accompanying label information before use
- store at 20° to 25°C (68° to 77°F)
- tamper-evident: do not use if the blue band around the capsule is missing or broken. Do not use if foil inner seal imprinted with "Sealed for your protection" is missing, open or broken.
- keep product out of high heat and humidity
- protect product from moisture

Inactive ingredients

citric acid anhydrous, croscarmellose sodium, FD&C blue #1 aluminum lake, gelatin, magnesium stearate, polysorbate 80, potassium sorbate, propylene glycol, shellac, sodium lauryl sulphate and titanium dioxide.

Questions or comments?

Call 1-855-274-4122

How Omeprazole and Sodium Bicarbonate Capsules, 20 mg/1100 mg
Works For Your Frequent Heartburn
Omeprazole and Sodium Bicarbonate Capsules, 20 mg/1100 mg works differently from other OTC heartburn products, such as antacids and other acid reducers. Omeprazole and Sodium Bicarbonate Capsules stops acid production at the source - the acid pump that produces stomach acid. Omeprazole and Sodium Bicarbonate Capsules is to be used once a day (every 24 hours), every day for 14 days.

TIPS FOR MANAGING HEARTBURN

- Do not lie flat or bend over soon after eating
- Do not eat late at night or just before bedtime
- Certain foods or drinks are more likely to cause heartburn, such as rich, spicy, fatty and fried foods, chocolate, caffeine, alcohol and even some fruits and vegetables
- Eat slowly and do not eat big meals
- If you are overweight, lose weight
- If you smoke, quit smoking
- Raise the head of your bed
- Wear loose-fitting clothing around your stomach

Distributed by:
AUROHEALTH LLC
279 Princeton-Hightstown Road
East Windsor, NJ 08520
Made in India
Code: TS/DRUGS/22/2009

PACKAGE LABEL-PRINCIPAL DISPLAY PANEL - 20 mg/1100 mg (14 Capsules Container Label)

AUROHEALTH
NDC 58602-725-05
CLINICALLY PROVEN TO
Treats Frequent Heartburn
Omeprazole and Sodium
Bicarbonate Capsules
• Omeprazole 20 mg / Acid Reducer
• Sodium Bicarbonate 1100 mg /
Allows Absorption of this Omeprazole Product
14 Capsules
One 14-Day Course of Treatment
May Take 1 to 4 days for full effect

PACKAGE LABEL-PRINCIPAL DISPLAY PANEL - 20 mg/1100 mg (14 Capsules Container Carton Label)

AUROHEALTH
NDC 58602-725-05
*Compare to Zegerid OTC® Capsules
Active Ingredients

CLINICALLY PROVEN TO
Treats Frequent Heartburn

Omeprazole and Sodium
Bicarbonate Capsules
• Omeprazole 20 mg / Acid Reducer
• Sodium Bicarbonate 1100 mg /
Allows Absorption of this Omeprazole Product

24 Hour

Actual Size
14 Capsules
One 14-Day Course of Treatment
May Take 1 to 4 days for full effect